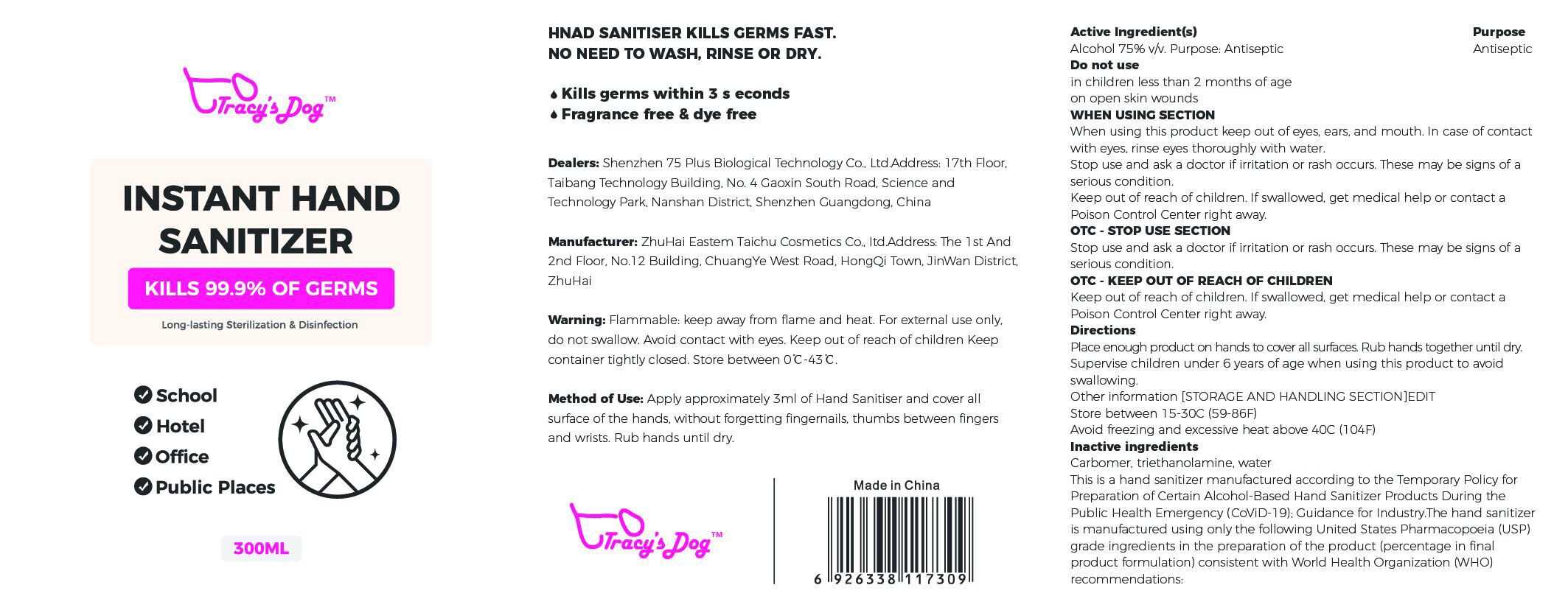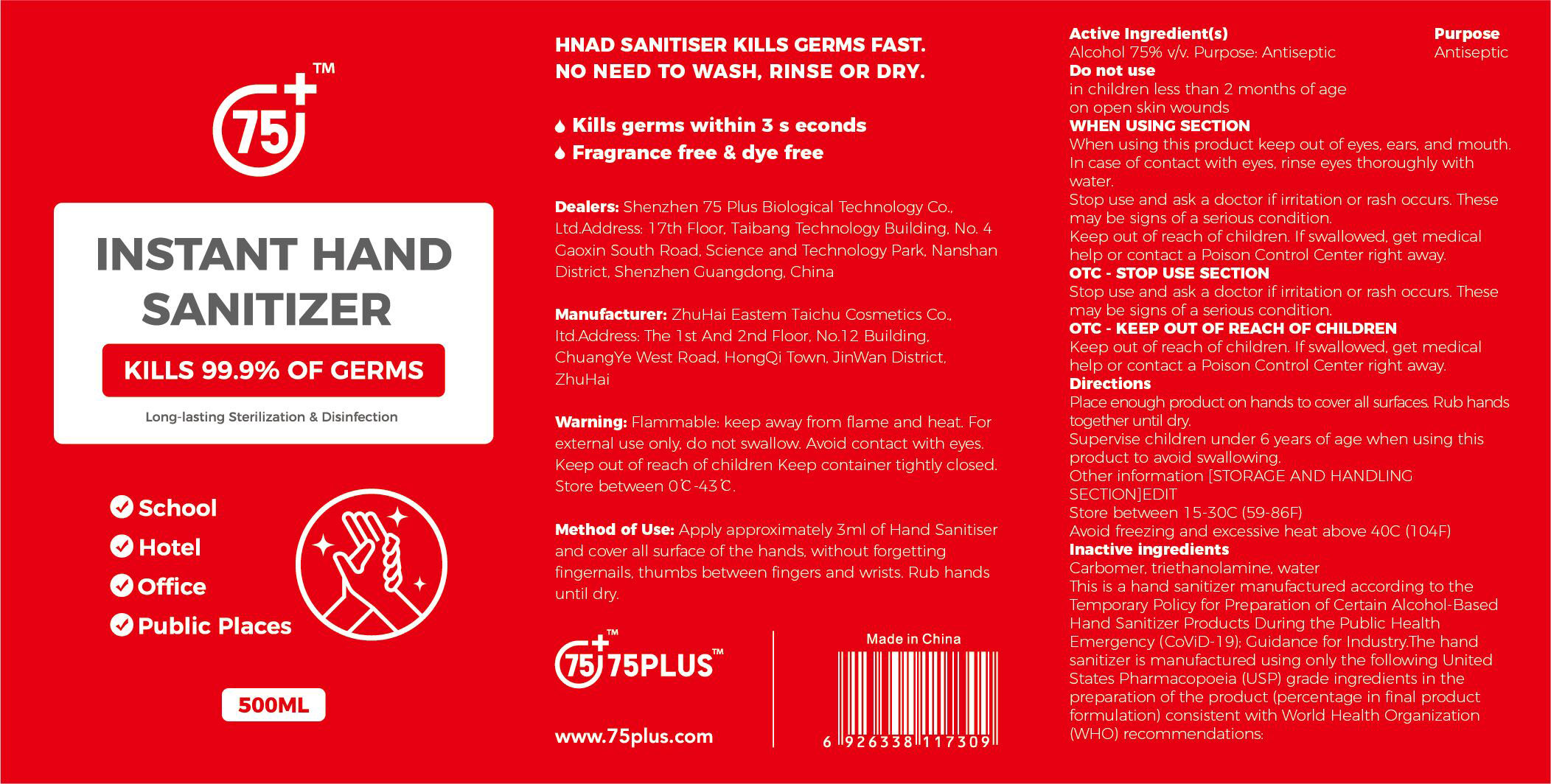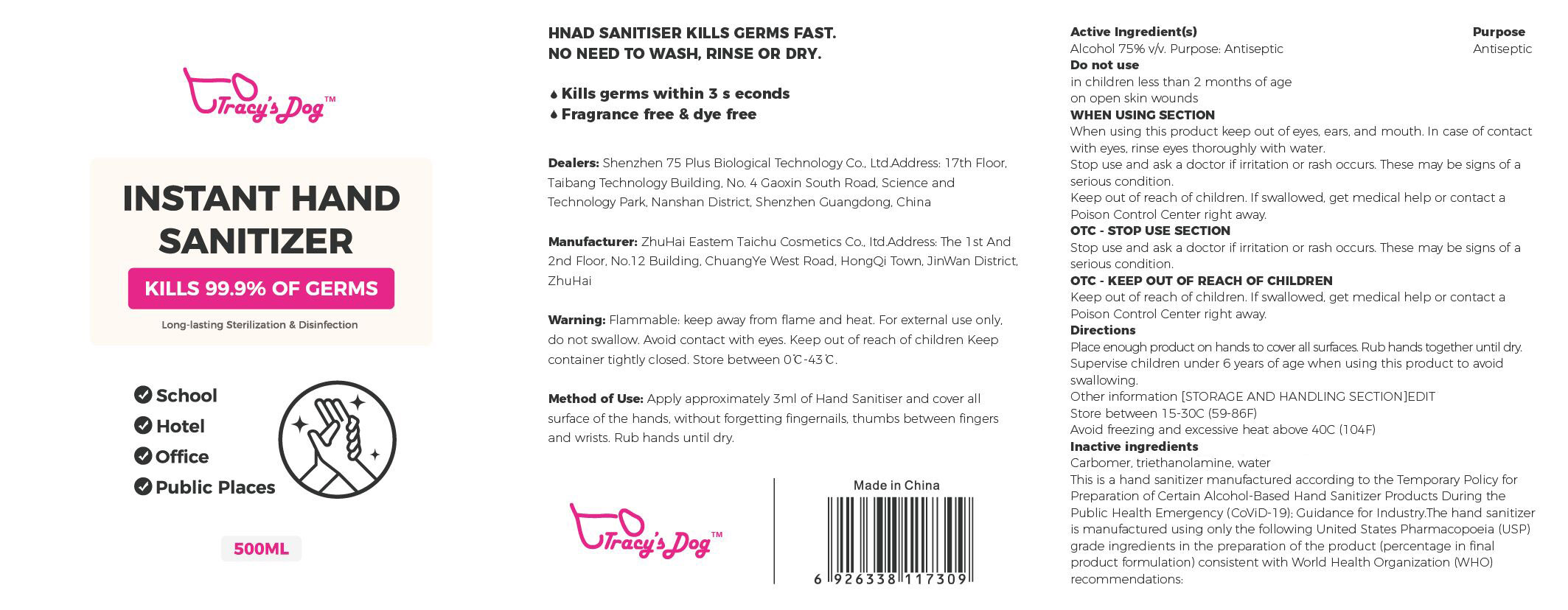 DRUG LABEL: INSTANT HAND SANITIZER
NDC: 79610-001 | Form: LIQUID
Manufacturer: ZHUHAI EASTERN TAICHU COSMETICS CO.,LTD
Category: otc | Type: HUMAN OTC DRUG LABEL
Date: 20200713

ACTIVE INGREDIENTS: ALCOHOL 75 mL/100 mL
INACTIVE INGREDIENTS: CARBOMER HOMOPOLYMER, UNSPECIFIED TYPE; TROLAMINE; WATER

INSTANT HAND SANITIZER

Active Ingredient(s)

Alcohol 75% v/v. Purpose: Antiseptic

Purpose

Antiseptic

Use

Apply approximately 3ml of Hand Sanitiser and cover all surface of the hands. without forgetting fingernails. thumbs between Angers and wrists. Rub hands until dry.

Warnings

Flammable: keep away from flame and heat. For external use only. do not swallow. Avoid contact with eyes. Keep out of reach of children Keep container tightly closed. Store between 0°C-43 °C.

Do not use

in children less than 2 months of age

on open skin wounds

When using this product keep out of eyes. ears. and mouth.
In case of contact with eyes. rinse eyes thoroughly with water.

Stop use and ask a doctor if irritation or rash occurs. These may be signs of a serious condition.

Keep out of reach of children. If swallowed. get medical help or contact a Poison Control Center right away.

Stop use and ask a doctor if irritation or ras h occurs. These may be signs of a serious condition.

Keep out of reach of children . If swallowed, get medical help or contact a Poison Control Center right away.

Directions

Place enough product on hands to cover all surfaces. Rub hands together until dry.

Supervise children under 6 years of age when using this product to avoid swaLlowing.

Inactive ingredients

Carbomer. triethanolamine. water